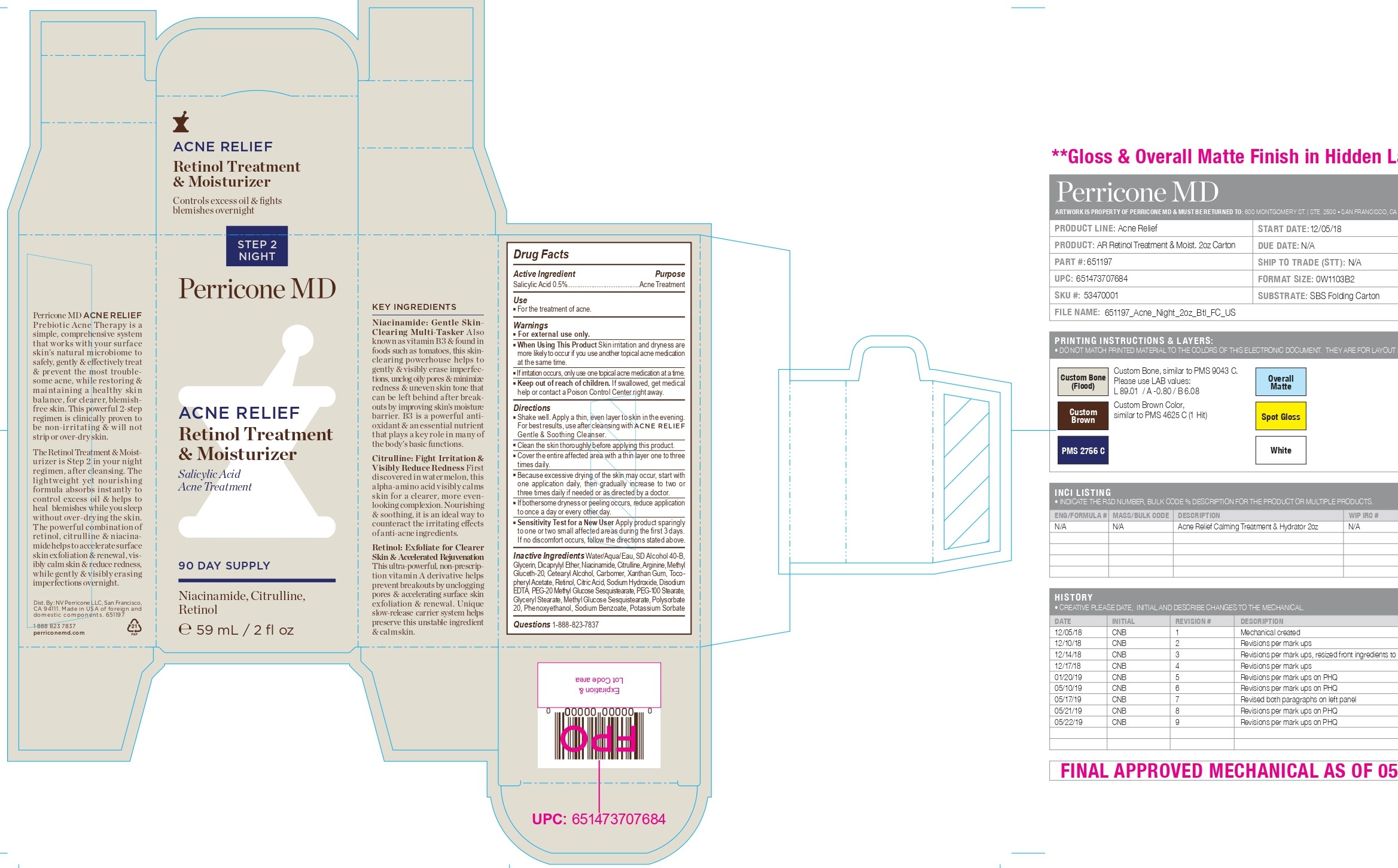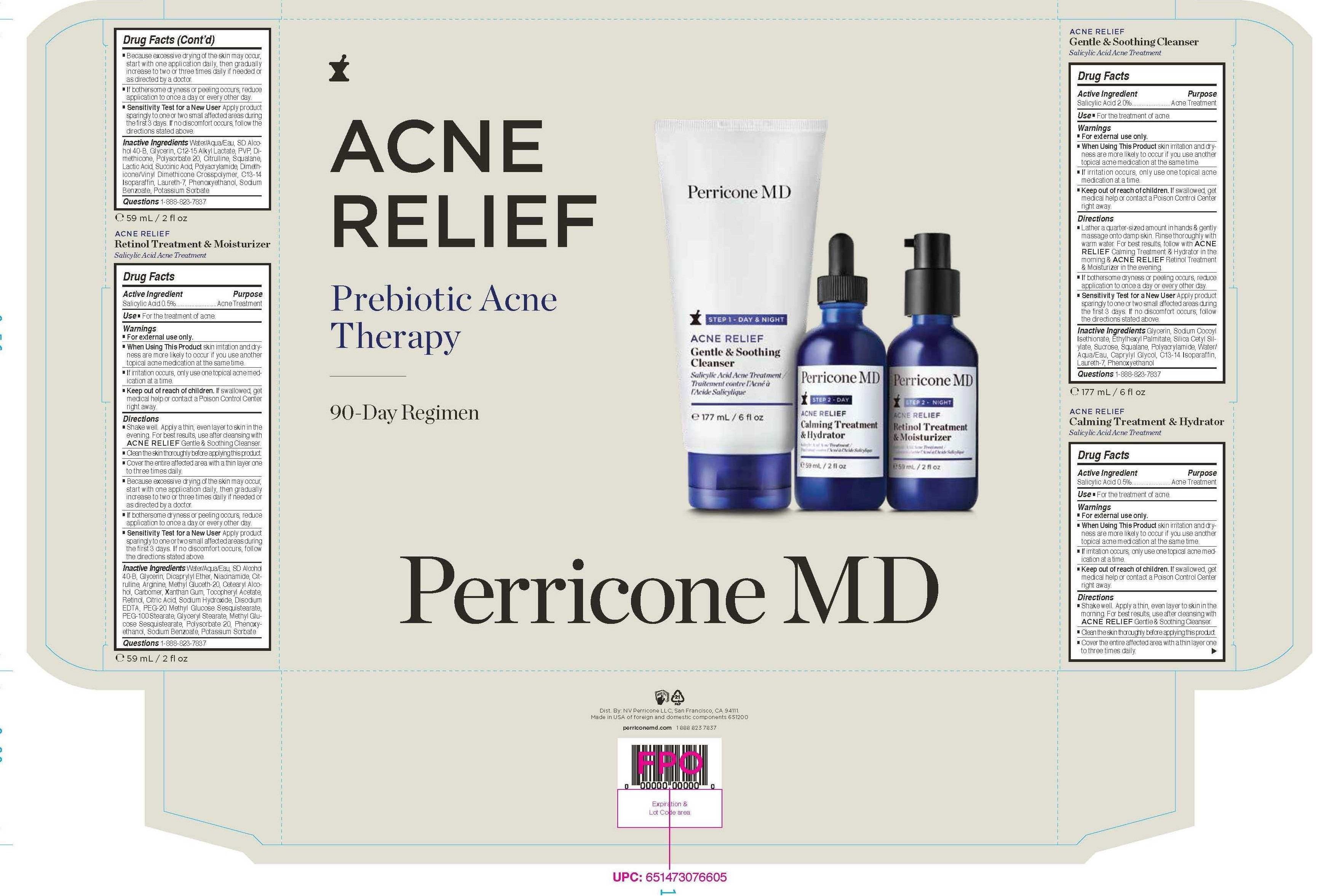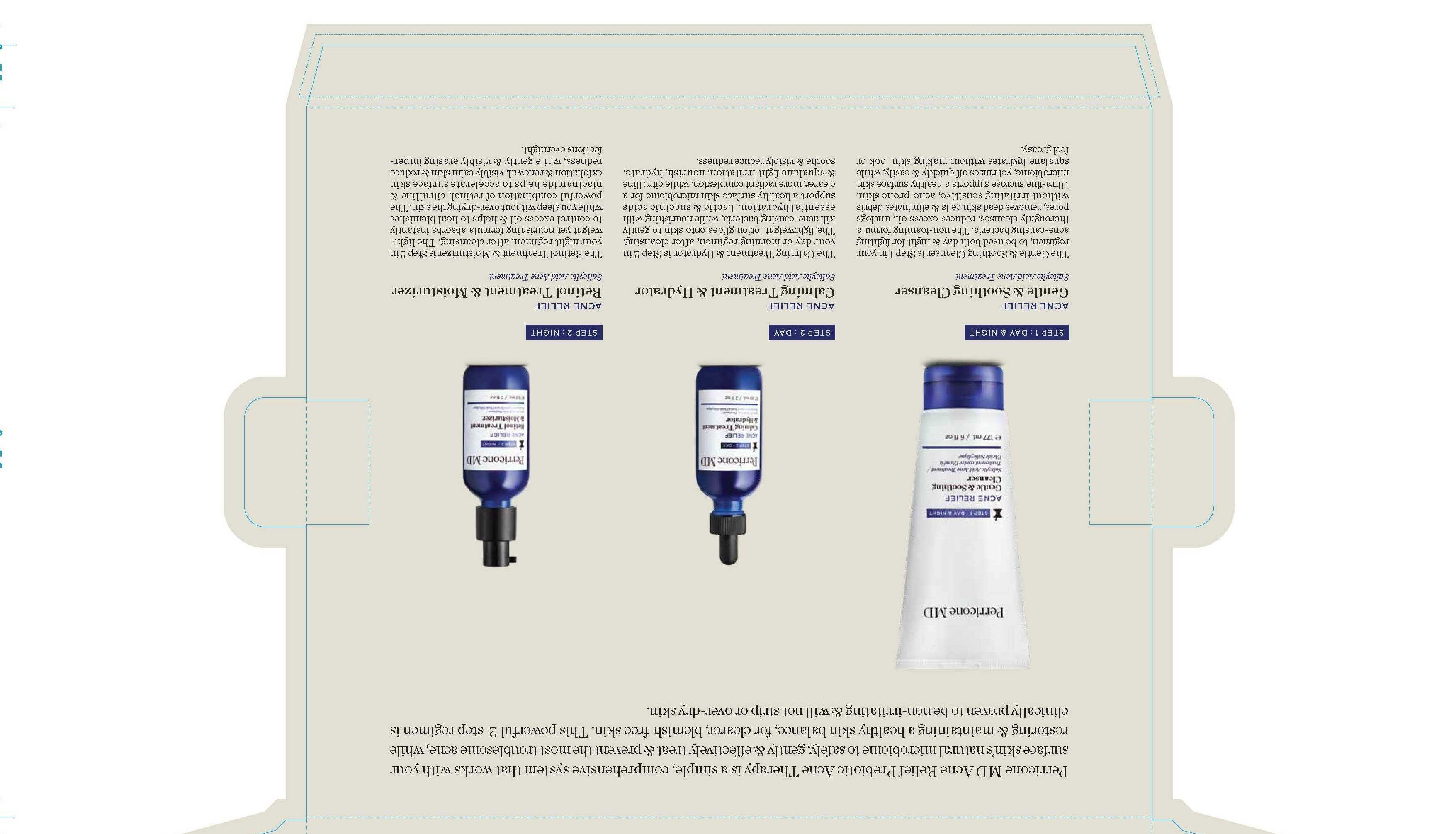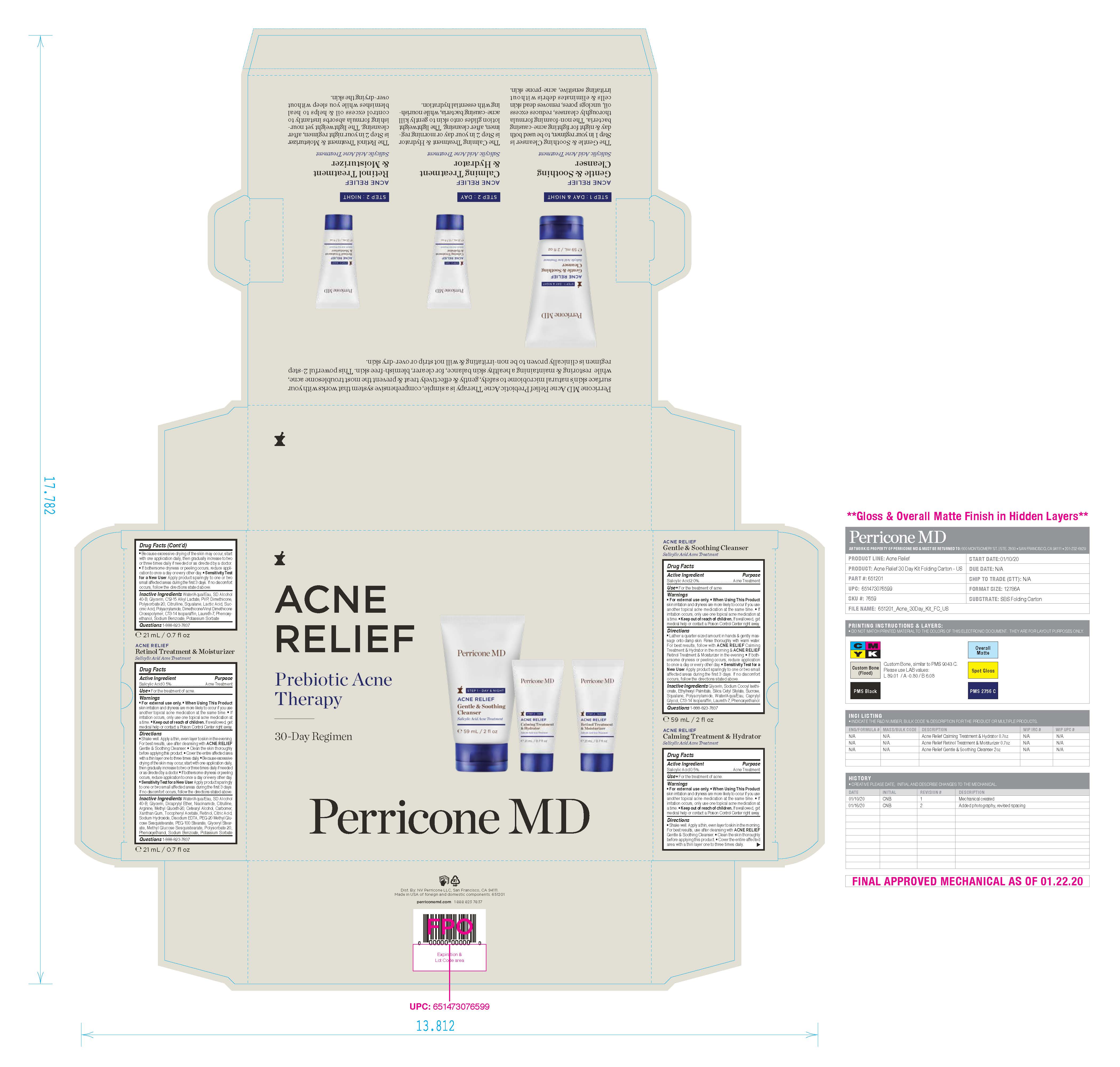 DRUG LABEL: Perricone MD Acne Relief Retinol Treatment and Moisturizer
NDC: 84448-537 | Form: CREAM
Manufacturer: THG Beauty USA LLC
Category: otc | Type: HUMAN OTC DRUG LABEL
Date: 20251021

ACTIVE INGREDIENTS: SALICYLIC ACID 0.5 g/100 mL
INACTIVE INGREDIENTS: WATER; ALPHA-TOCOPHEROL ACETATE; POLYSORBATE 20; PEG-20 METHYL GLUCOSE SESQUISTEARATE; METHYL GLUCOSE SESQUISTEARATE; PHENOXYETHANOL; XANTHAN GUM; CETOSTEARYL ALCOHOL; PEG-100 STEARATE; NIACINAMIDE; RETINOL; EDETATE DISODIUM; SODIUM BENZOATE; ALCOHOL; CITRULLINE; CARBOMER HOMOPOLYMER, UNSPECIFIED TYPE; METHYL GLUCETH-20; SODIUM HYDROXIDE; GLYCERYL STEARATE SE; POTASSIUM SORBATE; GLYCERIN; DICAPRYLYL ETHER; ARGININE; CITRIC ACID MONOHYDRATE

ACTIVE INGREDIENT

Salicylic Acid 0.5%

PURPOSE

Acne Treatment

INDICATIONS AND USAGE

■ For the treatment of acne.

WARNINGS

■ For external use only.

■ When Using This Product Skin irritation and dryness are more likely to occur if you use another topical acne medication at the same time.
■ If irritation occurs, only use one topical acne medication at a time.

■ Keep out of reach of children. If swallowed, get medical help or contact a Poison Control Center right away.

Directions
■ Shake well. Apply a thin, even layer to skin in the evening.
For best results, use after cleansing with ACNE RELIEF
Gentle & Soothing Cleanser.
■ Clean the skin thoroughly before applying this product.
■ Cover the entire affected area with a thin layer one to three
times daily.
■ Because excessive drying of the skin may occur, start with
one application daily, then gradually increase to two or
three times daily if needed or as directed by a doctor.
■ If bothersome dryness or peeling occurs, reduce application
to once a day or every other day.
■ Sensitivity Test for a New User Apply product sparingly
to one or two small affected areas during the first 3 days.
If no discomfort occurs, follow the directions stated above.

INACTIVE INGREDIENT

Water/Aqua/Eau, SD Alcohol 40-B, Glycerin, Dicaprylyl Ether, Niacinamide, Citrulline, Arginine, Methyl Gluceth-20, Cetearyl Alcohol, Carbomer, Xanthan Gum, Tocopheryl Acetate, Retinol, Citric Acid, Sodium Hydroxide, Disodium EDTA, PEG-20 Methyl Glucose Sesquistearate, PEG-100 Stearate, Glyceryl Stearate, Methyl Glucose Sesquistearate, Polysorbate 20, Phenoxyethanol, Sodium Benzoate, Potassium Sorbate

QUESTIONS

1-888-823-7837